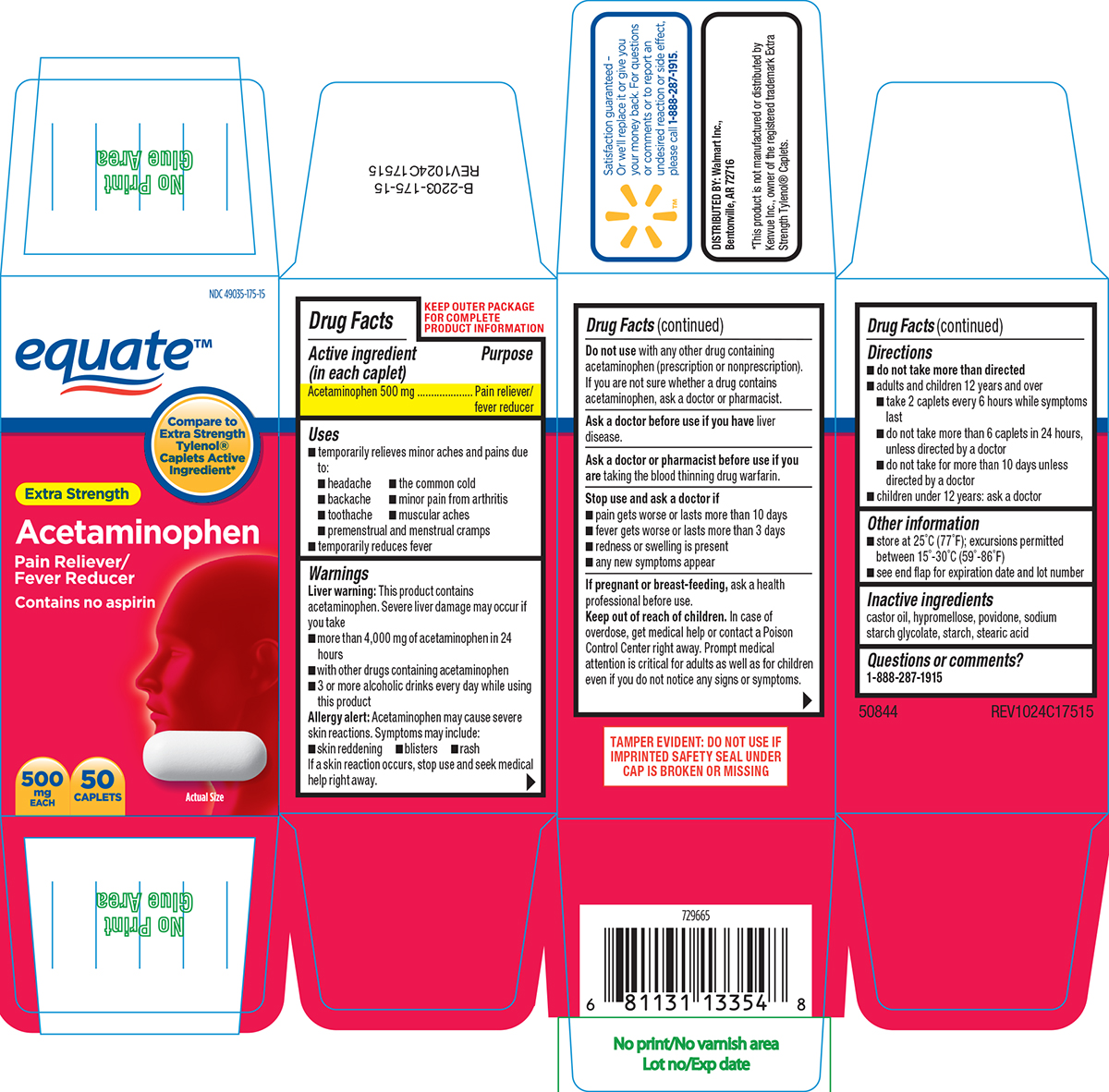 DRUG LABEL: Acetaminophen
NDC: 49035-175 | Form: TABLET, FILM COATED
Manufacturer: Wal-Mart Stores Inc
Category: otc | Type: HUMAN OTC DRUG LABEL
Date: 20250915

ACTIVE INGREDIENTS: ACETAMINOPHEN 500 mg/1 1
INACTIVE INGREDIENTS: CASTOR OIL; HYPROMELLOSE, UNSPECIFIED; POVIDONE, UNSPECIFIED; SODIUM STARCH GLYCOLATE TYPE A POTATO; STARCH, CORN; STEARIC ACID

Pain Reliever

Active ingredient (in each caplet)

Acetaminophen 500 mg

Purpose

Pain reliever/fever reducer

Uses

- temporarily relieves minor aches and pains due to:
  - headache
  - the common cold
  - backache
  - minor pain from arthritis
  - toothache
  - muscular aches
  - premenstrual and menstrual cramps
- temporarily reduces fever

Warnings

Liver warning: This product contains acetaminophen. Severe liver damage may occur if you take

- more than 4,000 mg of acetaminophen in 24 hours
- with other drugs containing acetaminophen
- 3 or more alcoholic drinks every day while using this product

Allergy alert: Acetaminophen may cause severe skin reactions. Symptoms may include:

- skin reddening
- blisters
- rash

If a skin reaction occurs, stop use and seek medical help right away.

Do not use

with any other drug containing acetaminophen (prescription or nonprescription). If you are not sure whether a drug contains acetaminophen, ask a doctor or pharmacist.

Ask a doctor before use if you have

liver disease.

Ask a doctor or pharmacist before use if you are

taking the blood thinning drug warfarin.

Stop use and ask a doctor if

- pain gets worse or lasts more than 10 days
- fever gets worse or lasts more than 3 days
- any new symptoms appear
- redness or swelling is present

If pregnant or breast-feeding,

ask a health professional before use.

Keep out of reach of children.

In case of overdose, get medical help or contact a Poison Control Center right away. Prompt medical attention is critical for adults as well as for children even if you do not notice any signs or symptoms.

Directions

- do not take more than directed
- adults and children 12 years and over
  - take 2 caplets every 6 hours while symptoms last
  - do not take more than 6 caplets in 24 hours, unless directed by a doctor
  - do not take for more than 10 days unless directed by a doctor
- children under 12 years: ask a doctor

Other information

- store at 25ºC (77ºF); excursions permitted between 15º-30ºC (59º-86ºF)
- see end flap for expiration date and lot number

Inactive ingredients

castor oil, hypromellose, povidone, sodium starch glycolate, starch, stearic acid

Questions or comments?

1-888-287-1915

Principal Display Panel

NDC 49035-175-15

equate™

Compare to
Extra Strength
Tylenol®
Caplets Active
Ingredient*

Extra Strength
Acetaminophen

Pain Reliever/
Fever Reducer

Contains no aspirin

500
mg
EACH

50
CAPLETS

Actual Size

*This product is not manufactured or distributed by
Kenvue Inc., owner of the registered trademark Extra
Strength Tylenol® Caplets.

Satisfaction guaranteed -
Or we'll replace it or give you
your money back. For questions
or comments or to report an
undesired reaction or side effect,
please call 1-888-287-1915.

DISTRIBUTED BY: Walmart Inc.,
Bentonville, AR 72716

TAMPER EVIDENT: DO NOT USE IF
IMPRINTED SAFETY SEAL UNDER
CAP IS BROKEN OR MISSING

50844 REV1024C17515

Equate 44-175